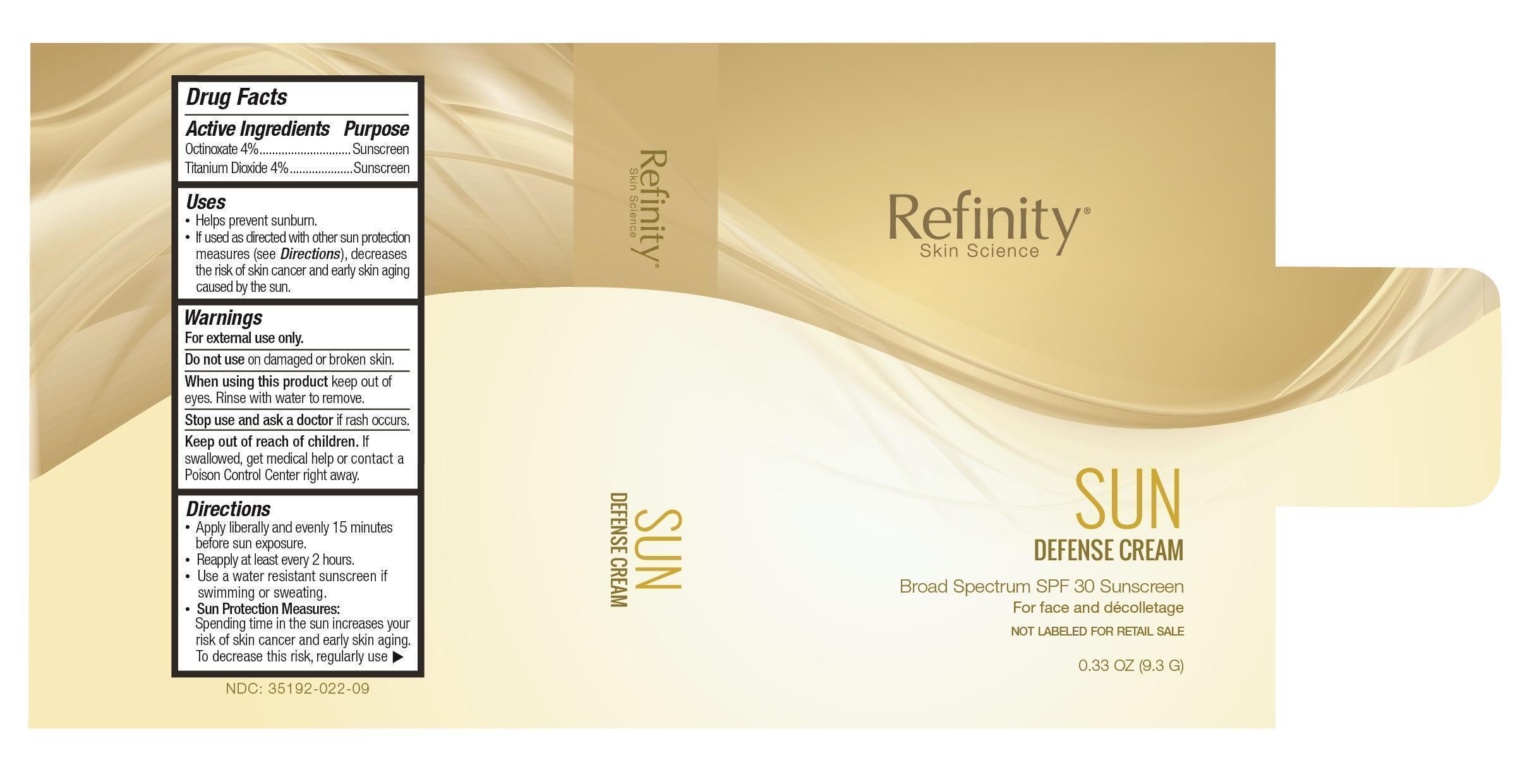 DRUG LABEL: Sun Defense Cream
NDC: 35192-022 | Form: LOTION
Manufacturer: CA-BOTANA INTERNATIONAL
Category: otc | Type: HUMAN OTC DRUG LABEL
Date: 20150901

ACTIVE INGREDIENTS: OCTINOXATE 0.372 g/0.375 g; TITANIUM DIOXIDE 0.372 g/0.375 g
INACTIVE INGREDIENTS: HYALURONIC ACID; ALOE VERA LEAF; ALUMINUM STARCH OCTENYLSUCCINATE; ASCORBIC ACID; ASCORBYL PALMITATE; BORON NITRIDE; CAMELLIA SINENSIS FLOWER; CAPRYLIC/CAPRIC MONO/DIGLYCERIDES; STEARYL ALCOHOL; CETYL ALCOHOL; CETEARYL ISONONANOATE; CITRIC ACID MONOHYDRATE; COCO-CAPRYLATE; ETHYLHEXYLGLYCERIN; GLYCERIN; NIACIN; PANTHENOL; PHENOXYETHANOL; POTASSIUM SORBATE; PROPANEDIOL; ROSMARINUS OFFICINALIS FLOWERING TOP OIL; SORBITAN MONOSTEARATE; TOCOPHEROL; GRAPE SEED OIL; XANTHAN GUM; WATER

Warning and Precautions Section

For external use only. Do not use on damaged or broken skin. When using this product keep out of eyes. Rinse with water to remove. Stop use and ask a doctor if rash occurs. Keep out of reach of children. If product is swallowed, get medical help or contact a poison control center right away.

DOSAGE & ADMINISTRATION SECTION

Helps prevent sunburn. If used as directed with other sun protection measured decreases the risk of skin cancer and early skin aging caused by the sun. Apply liberally 15 minutes before sun exposure. Use a water resistant sunscreen if swimming or sweating. Reapply: at least 2 hours. Children under 6 months: Ask a doctor. Sun protection measurements. Spending time in the sun increases your risk of skin cancer and early skin aging. To decrease this risk, regularly use a sunscreen with a broad spectrum SPF of 15 or higher and other sun protection measures including: limit time in the sun, especially from 10 a.m - 2 p.m. Wear long-sleeve shirts, pants, hats, and sunglasses. Protect this product from excessive heat and direct sun

INACTIVE INGREDIENT SECTION

ALOE VERA LEAF

ALUMINUM STARCH OCTENYLSUCCINATE

ASCORBIC ACID

ASCORBYL PALMITATE

BORON NITRIDE

CAMELLIA SINENSIS FLOWER

CAPRYLIC/CAPRIC MONO/DIGLYCERIDES

STEARYL ALCOHOL

CETYL ALCOHOL

CETEARYL ESONONANOATE

CITRIC ACID MONOHYDRATE

CITRUS AURANTIUM FLOWER OIL

COCO-CAPRYLATE

ETHYLHEXYLGLYCERIN

GLYCERIN

SUNFLOWER OIL

NEACEN

PANTHENOL

PHENOXYETHANOL

EGG PHOSPHOLIPIDS

POTASSIUM SORBATE

PROPANEDIOL

ROSMARINUS OFFICINALIS FLOWERING TOP OIL

PEG-9 DIGLYCIDYL ETHER/SODIUM HYALURONATE CROSSPOLYMER

SORBITAN STEARATE

TOCOPHEROL

GRAPE SEED OIL

XANTHAN GUM

WATER

OTC - ACTIVE INGREDIENT SECTION

OCTINOXATE

TITANIUM DIOXIDE

keep out of reach of children section

For external use only.

Avoid contact with eyes.

Keep out of reach of children.

Do not apply to open wounds.

STOP USE AND ask a doctor if condition worsens or

symptoms persist for more than seven days, discontinue

use of the product.